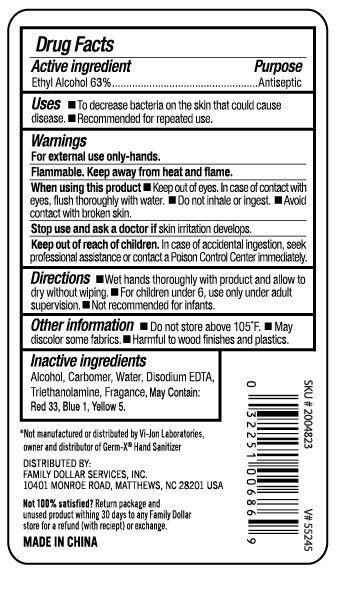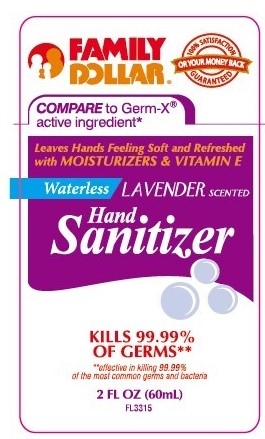 DRUG LABEL: Waterless Lavender Scented Hand Sanitizer
NDC: 55319-500 | Form: GEL
Manufacturer: Family Dollar  Services Inc. 
Category: otc | Type: HUMAN OTC DRUG LABEL
Date: 20110328

ACTIVE INGREDIENTS: ALCOHOL 63 mL/100 mL
INACTIVE INGREDIENTS: ALCOHOL; WATER; EDETATE DISODIUM ; TROLAMINE; D&C RED NO. 33; FD&C BLUE NO. 1; FD&C YELLOW NO. 5

Waterless Lavender Scented Hand Sanitizer

Drug Facts

Active Ingredient

Ethyl Alcohol 63%

Purpose

Antiseptic

Uses

- To decrease bacteria on the skin that could cause disease.
- Recommended for repeated use.

Warnings

For external use only - hands.

STORAGE AND HANDLING

Flammable. Keep away from heat and flame.

When using this product

- Keep out of eyes. In case of contact with eyes, flush thoroughly with water.
- Do not inhale or ingest.
- Avoid contact with broken skin.

Stop use and ask a doctor if skin irritation develops.

Keep out of reach of children. In case of accidental ingestion, seek professional assistance or contact a Poison Control Center immediately.

Directions

- Wet hands thoroughly with product and allow to dry without wiping.
- For children under 6, use only under adult supervision.
- Not recommended for infants.

Other information

- Do not store above 105 degrees F
- May discolor some fabrics.
- Harmful to wood finishes and plastics.

Inactive ingredients

Alcohol, Carbomer, Water, Disodium EDTA, Triethanolamine, Fragrance, May Contain: Red 33, Blue 1, Yellow 5.

*Not manufactured or distributed by VI-Jon Laboratories, owner and distributor of Germ-X Hand Sanitizer

DISTRIBUTED BY:

FAMILY DOLLAR SERVICES, INC.

10401 MONROE ROAD, MATTHEWS, NC 28201 USA

Not 100% satisfied? Return package and unused product within 30 days to any Family Dollar store for a refund (with receipt) or exchange.

MADE IN CHINA

PACKAGE LABEL

FAMILY DOLLAR
100% SATISFACTION GUARANTEED
OR YOUR MONEY BACK
COMPARE to Germ-X active ingredient
Leaves Hands Feeling Soft and Refreshed with MOISTURIZERS AND VITAMINE E
Waterless LAVENDER scented
Hand Sanitizer
Kills 99.99 percent OF Germs
effective in killing 99.99 percent of the most common germs and bacteria
2 FL OZ (60ml)